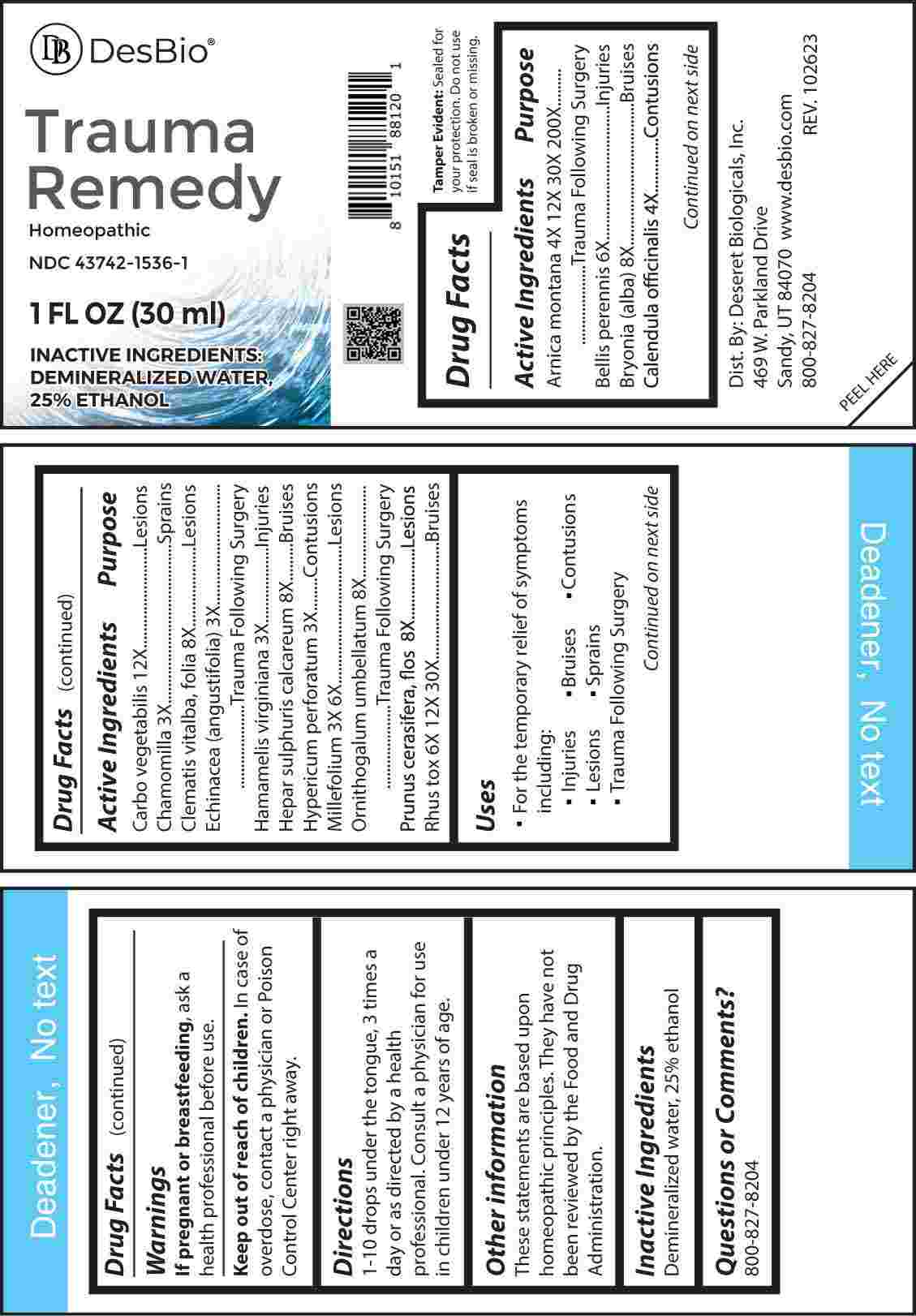 DRUG LABEL: Trauma Remedy
NDC: 43742-1536 | Form: LIQUID
Manufacturer: Deseret Biologicals, Inc.
Category: homeopathic | Type: HUMAN OTC DRUG LABEL
Date: 20240307

ACTIVE INGREDIENTS: MATRICARIA CHAMOMILLA WHOLE 3 [hp_X]/1 mL; ECHINACEA ANGUSTIFOLIA WHOLE 3 [hp_X]/1 mL; HAMAMELIS VIRGINIANA ROOT BARK/STEM BARK 3 [hp_X]/1 mL; HYPERICUM PERFORATUM WHOLE 3 [hp_X]/1 mL; ACHILLEA MILLEFOLIUM WHOLE 3 [hp_X]/1 mL; CALENDULA OFFICINALIS FLOWERING TOP 4 [hp_X]/1 mL; ARNICA MONTANA WHOLE 4 [hp_X]/1 mL; BELLIS PERENNIS WHOLE 6 [hp_X]/1 mL; TOXICODENDRON PUBESCENS LEAF 6 [hp_X]/1 mL; BRYONIA ALBA ROOT 8 [hp_X]/1 mL; CLEMATIS VITALBA TOP 8 [hp_X]/1 mL; CALCIUM SULFIDE 8 [hp_X]/1 mL; ORNITHOGALUM UMBELLATUM WHOLE 8 [hp_X]/1 mL; PRUNUS CERASIFERA FLOWER 8 [hp_X]/1 mL; ACTIVATED CHARCOAL 12 [hp_X]/1 mL
INACTIVE INGREDIENTS: WATER; ALCOHOL

DRUG FACTS:

ACTIVE INGREDIENTS:

Arnica Montana 4X, 12X, 30X, 200X, Bellis Perennis 6X, Bryonia (Alba) 8X, Calendula Officinalis 4X, Carbo Vegetabilis 12X, Chamomilla 3X, Clematis Vitalba, Folia 8X, Echinacea (Angustifolia) 3X, Hamamelis Virginiana 3X, Hepar Sulphuris Calcareum 8X, Hypericum Perforatum 3X, Millefolium 3X, 6X, Ornithogalum Umbellatum 8X, Prunus Cerasifera, Flos 8X, Rhus Tox 6X, 12X, 30X.

PURPOSE:

Arnica Montana – Trauma Following Surgery, Bellis Perennis - Injuries, Bryonia (Alba) - Bruises, Calendula Officinalis - Contusions, Carbo Vegetabilis - Lesions, Chamomilla - Sprains, Clematis Vitalba, Folia - Lesions, Echinacea (Angustifolia) – Trauma Following Surgery, Hamamelis Virginiana - Injuries, Hepar Sulphuris Calcareum - Bruises, Hypericum Perforatum - Contusions, Millefolium - Lesions, Ornithogalum Umbellatum – Trauma Following Surgery, Prunus Cerasifera, Flos - Lesions, Rhus Tox - Bruises

USES:

• For the temporary relief of symptoms including:

• Injuries • Bruises • Contusions • Lesions

• Sprains • Trauma Following Surgery

These statements are based upon homeopathic principles. They have not been reviewed by the Food and Drug Administration.

WARNINGS:

If pregnant or breast-feeding, ask a health professional before use.

Keep out of reach of children. In case of overdose, contact a physician or Poison Control Center right away.
Tamper Evident: Sealed for your protection. Do not use if seal is broken or missing.

KEEP OUT OF REACH OF CHILDREN:

In case of overdose, contact a physician or Poison Control Center right away.

DIRECTIONS:

1-10 drops under the tongue, 3 times a day or as directed by a health professional. Consult a physician for use in children under 12 years of age.

INACTIVE INGREDIENTS:

Demineralized water, 25% ethanol

QUESTIONS:

Dist. By: Deseret Biologicals, Inc.
469 W. Parkland Drive
Sandy, UT 84070

www.desbio.com

800-827-8204

PACKAGE LABEL DISPLAY:

Des Bio

Trauma

Remedy

Homeopathic

NDC 43742-1536-1

1 FL OZ (30 ml)